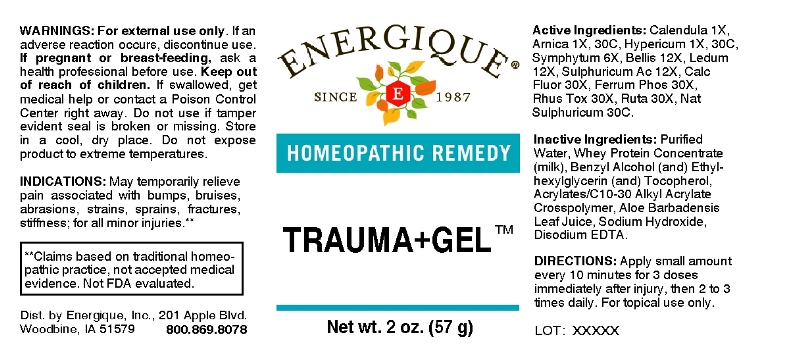 DRUG LABEL: Trauma plus Gel
NDC: 44911-0446 | Form: GEL
Manufacturer: Energique, Inc.
Category: homeopathic | Type: HUMAN OTC DRUG LABEL
Date: 20180208

ACTIVE INGREDIENTS: CALENDULA OFFICINALIS FLOWERING TOP 1 [hp_X]/1 g; ARNICA MONTANA 1 [hp_X]/1 g; HYPERICUM PERFORATUM 1 [hp_X]/1 g; COMFREY ROOT 6 [hp_X]/1 g; BELLIS PERENNIS 12 [hp_X]/1 g; LEDUM PALUSTRE TWIG 12 [hp_X]/1 g; SULFURIC ACID 12 [hp_X]/1 g; CALCIUM FLUORIDE 30 [hp_X]/1 g; FERROSOFERRIC PHOSPHATE 30 [hp_X]/1 g; TOXICODENDRON PUBESCENS LEAF 30 [hp_X]/1 g; RUTA GRAVEOLENS FLOWERING TOP 30 [hp_X]/1 g; SODIUM SULFATE 30 [hp_C]/1 g
INACTIVE INGREDIENTS: WATER; WHEY; BENZYL ALCOHOL; ETHYLHEXYLGLYCERIN; TOCOPHEROL; CARBOMER INTERPOLYMER TYPE A (ALLYL SUCROSE CROSSLINKED); ALOE VERA LEAF; SODIUM HYDROXIDE; EDETATE DISODIUM

Drug Facts:

ACTIVE INGREDIENTS:

Calendula Officinalis 1X, Arnica Montana 1X, 30C, Hypericum Perforatum 1X, 30C, Symphytum Officinale 6X, Bellis Perennis 12X, Ledum Palustre 12X, Sulphuricum Acidum 12X, Calcarea Fluorica 30X, Ferrum Phosphoricum 30X, Rhus Tox 30X, Ruta Graveolens 30X, Natrum Sulphuricum 30C.

INDICATIONS:

For temporary relief of pain associated with bumps, bruises, abrasions, strains, sprains, fractures, stiffness; for all minor injuries.**

**These statements are based upon traditional homeopathic practice. They have not been reviewed by the Food and Drug Administration.

WARNINGS:

For external use only. If an adverse reaction occurs, discontinue use.

If pregnant or breast-feeding, ask a health professional before use.

Keep out of reach of children. If swallowed, get medical help or contact a Poison Control Center right away.

Do not use if tamper evident seal is broken or missing.

Store in a cool, dry place. Do not expose product to extreme temperatures.

Keep out of reach of children. If swallowed, get medical help or contact a Poison Control Center right away.

DIRECTIONS:

Apply small amount every 10 minutes for 3 doses immediately after injury, then 2 to 3 times daily. For topical use only.

INDICATIONS:

For temporary relief of pain associated with bumps, bruises, abrasions, strains, sprains, fractures, stiffness; for all minor injuries.**

**These statements are based upon traditional homeopathic practice. They have not been reviewed by the Food and Drug Administration.

INACTIVE INGREDIENTS:

Purified Water, Whey Protein Concentrate (milk), Benzyl Alcohol, Ethylhexylglycerin, Tocopherol, Acrylates/C10-30 Alkyl Acrylate Crosspolymer (Carbopol (Ultrez 21), Aloe Barbadensis Leaf Juice (Aloe Vera 10X Concentrate), Sodium Hydroxide (Solution), Edetate Disodium (EDTA).

QUESTIONS:

Dist. by Energique, Inc., 201 Apple Blvd.
Woodbine, IA 51579 800.869.8078

PACKAGE LABEL DISPLAY:

ENERGIQUE

SINCE 1987

HOMEOPATHIC REMEDY

TRAUMA+GEL

Net wt. 2 oz. (57 g)